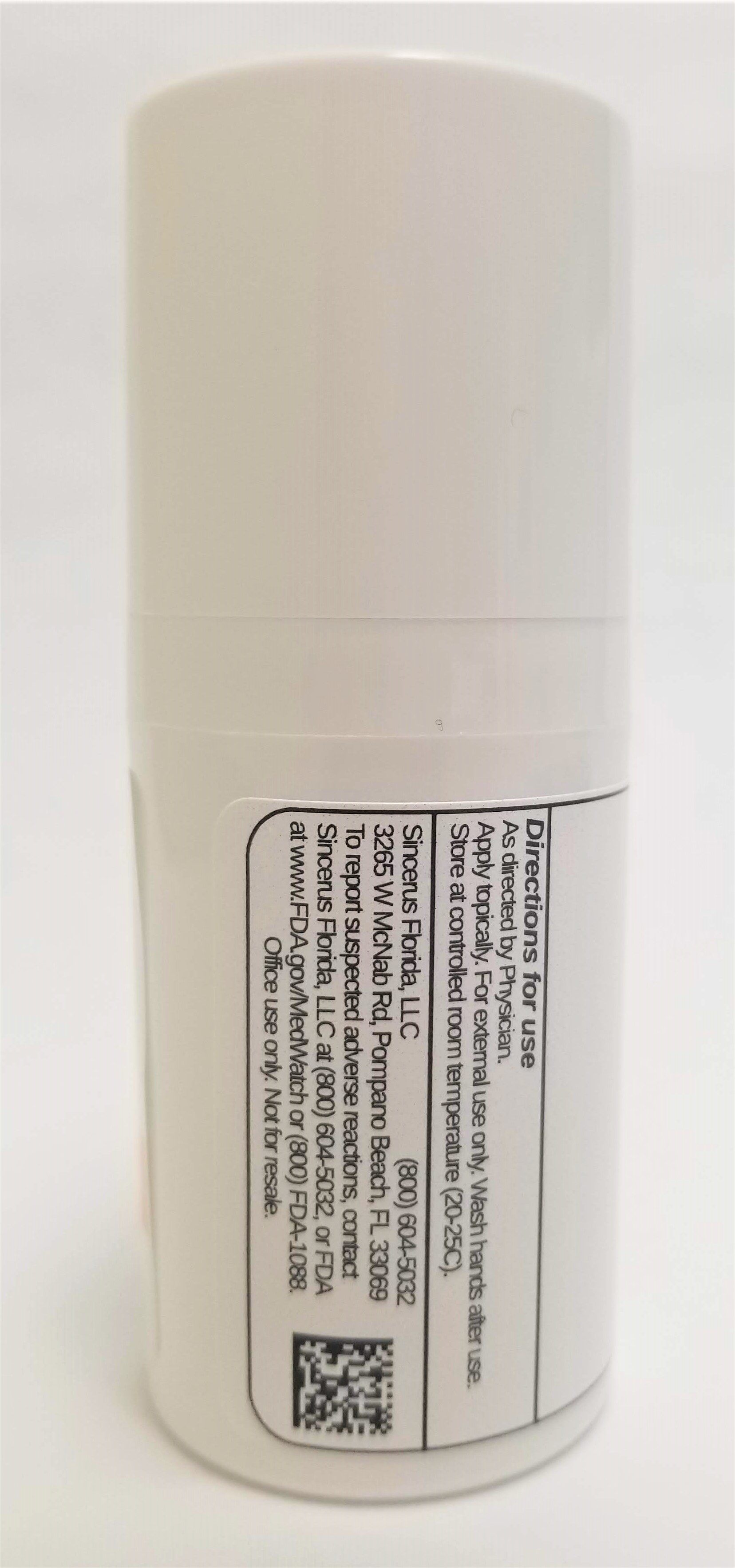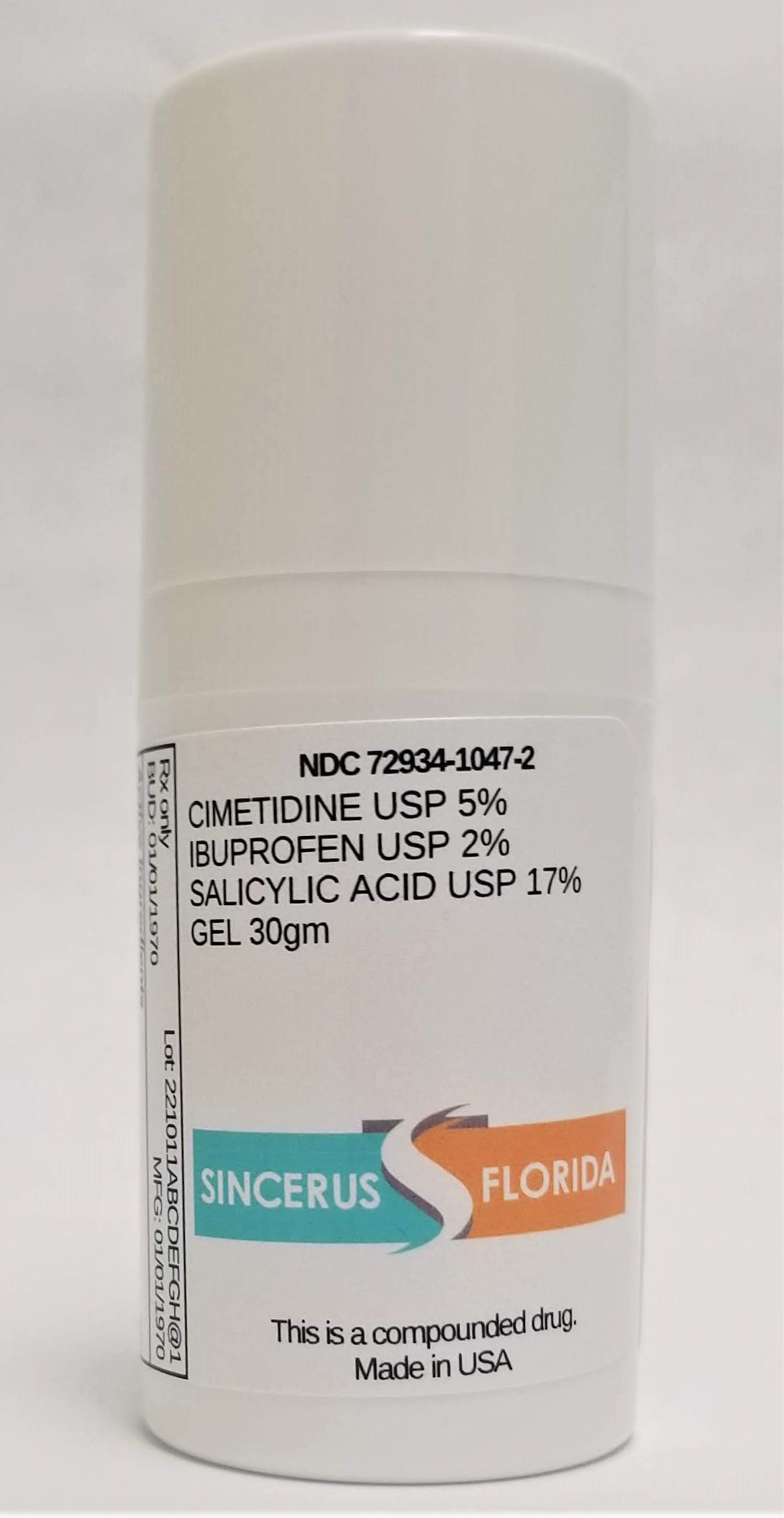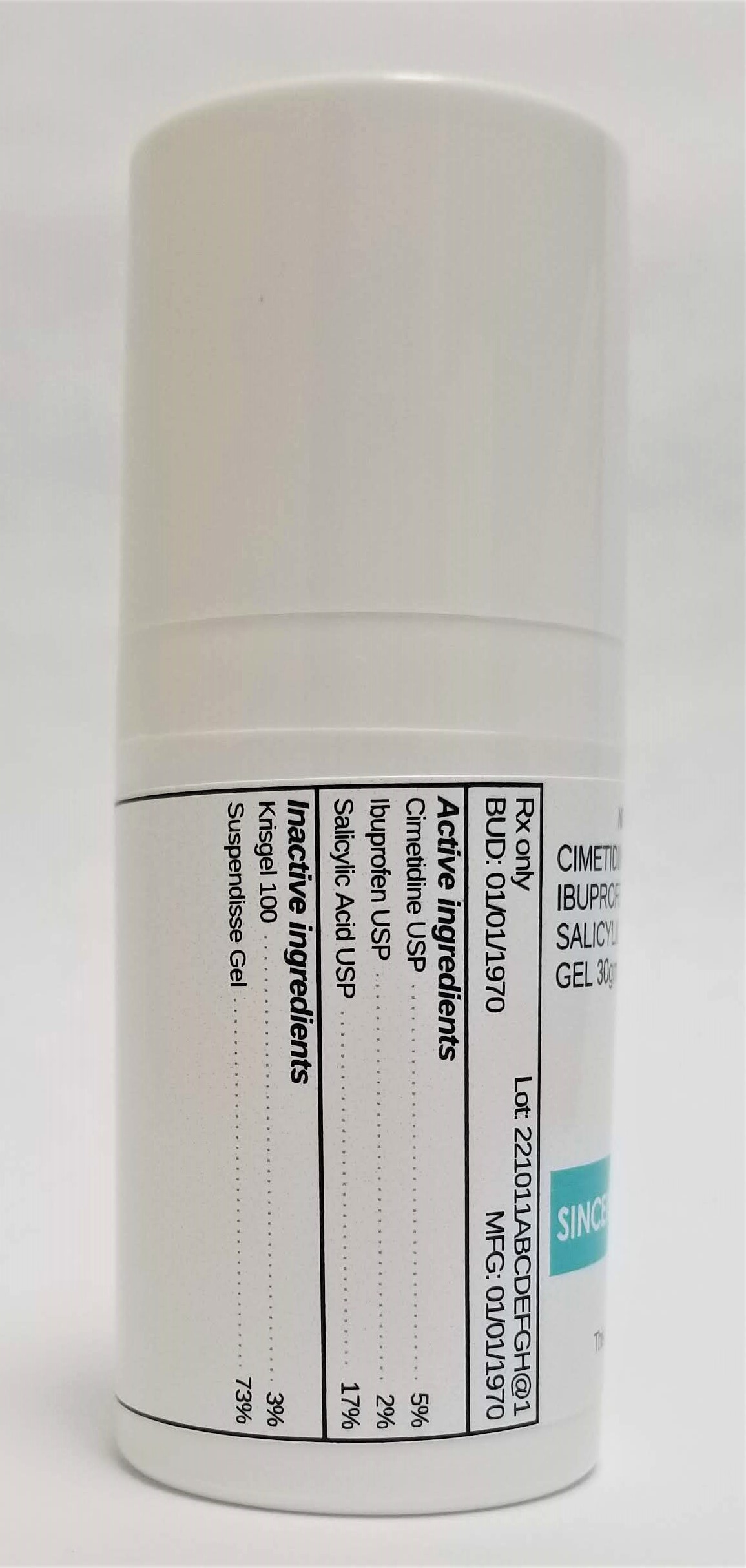 DRUG LABEL: CIMETIDINE 5% / IBUPROFEN 2% / SALICYLIC ACID 17%
NDC: 72934-1047 | Form: GEL
Manufacturer: Sincerus Florida, LLC
Category: prescription | Type: HUMAN PRESCRIPTION DRUG LABEL
Date: 20190517

ACTIVE INGREDIENTS: IBUPROFEN 2 g/100 g; CIMETIDINE 5 g/100 g; SALICYLIC ACID 17 g/100 g

CIMETIDINE 5% / IBUPROFEN 2% / SALICYLIC ACID 17%